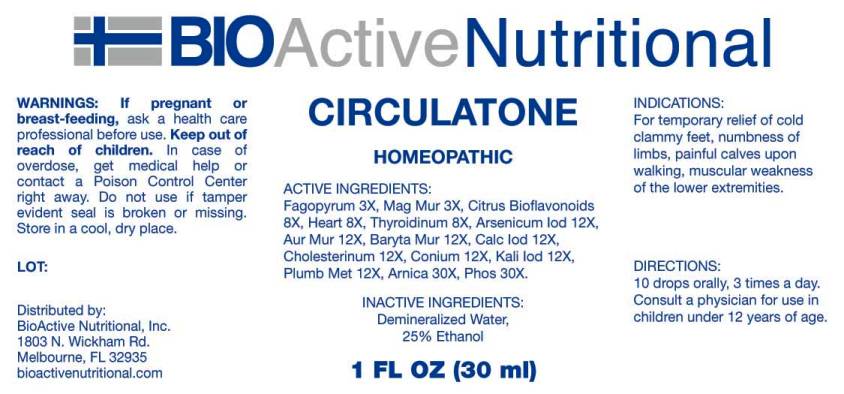 DRUG LABEL: Circulatone
NDC: 43857-0164 | Form: LIQUID
Manufacturer: BioActive Nutritional, Inc.
Category: homeopathic | Type: HUMAN OTC DRUG LABEL
Date: 20161110

ACTIVE INGREDIENTS: FAGOPYRUM ESCULENTUM 3 [hp_X]/1 mL; MAGNESIUM CHLORIDE 3 [hp_X]/1 mL; CITRUS BIOFLAVONOIDS 8 [hp_X]/1 mL; PORK HEART 8 [hp_X]/1 mL; SUS SCROFA THYROID 8 [hp_X]/1 mL; ARSENIC TRIIODIDE 12 [hp_X]/1 mL; GOLD TRICHLORIDE 12 [hp_X]/1 mL; BARIUM CHLORIDE DIHYDRATE 12 [hp_X]/1 mL; CALCIUM IODIDE 12 [hp_X]/1 mL; CHOLESTEROL 12 [hp_X]/1 mL; CONIUM MACULATUM FLOWERING TOP 12 [hp_X]/1 mL; POTASSIUM IODIDE 12 [hp_X]/1 mL; LEAD 12 [hp_X]/1 mL; ARNICA MONTANA 30 [hp_X]/1 mL; PHOSPHORUS 30 [hp_X]/1 mL
INACTIVE INGREDIENTS: WATER; ALCOHOL

Drug Facts:

ACTIVE INGREDIENTS:

Fagopyrum Esculentum 3X, Magnesia Muriatica 3X, Citrus Bioflavonoids 8X, Heart (Suis) 8X, Thyroidinum (Suis) 8X, Arsenicum Iodatum 12X, Aurum Muriaticum 12X, Baryta Muriatica 12X, Calcarea Iodata 12X, Cholesterinum 12X, Conium Maculatum 12X, Kali Iodatum 12X, Plumbum Metallicum 12X, Arnica Montana 30X, Phosphorus 30X.

INDICATIONS:

For temporary relief of cold clammy feet, numbness of limbs, painful calves upon walking, muscular weakness of the lower extremities.

WARNINGS:

If pregnant or breast-feeding, ask a health care professional before use.

Keep out of reach of children. In case of overdose, get medical help or contact a Poison Control Center right away.

Do not use if tamper evident seal is broken or missing.

Store in cool, dry place.

DIRECTIONS:

10 drops orally, 3 times a day. Consult a physician for use in children under 12 years of age.

INACTIVE INGREDIENTS:

Demineralized Water, 25% Ethanol.

Keep out of reach of children. In case of overdose, get medical help or contact a Poison Control Center right away.

INDICATIONS:

For temporary relief of cold clammy feet, numbness of limbs, painful calves upon walking, muscular weakness of the lower extremities.

QUESTIONS:

Distributed by:
BioActive Nutritional, Inc.
1803 N. Wickham Rd.
Melbourne, FL 32935
bioactivenutritional.com

PACKAGE LABEL DISPLAY:

BIOActive Nutritional

CIRCULATONE

HOMEOPATHIC

1 FL OZ (30 ml)